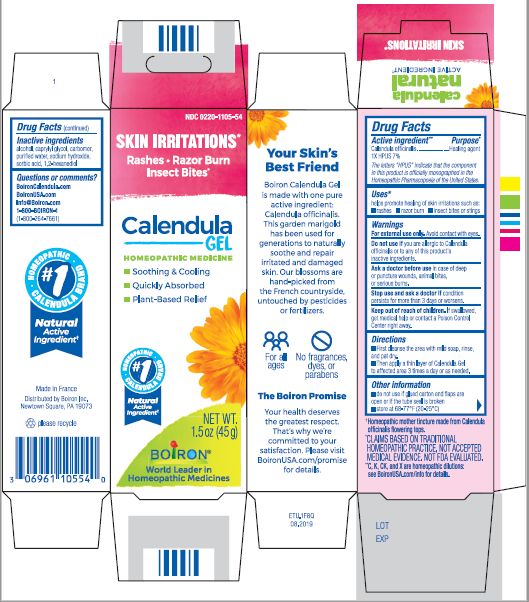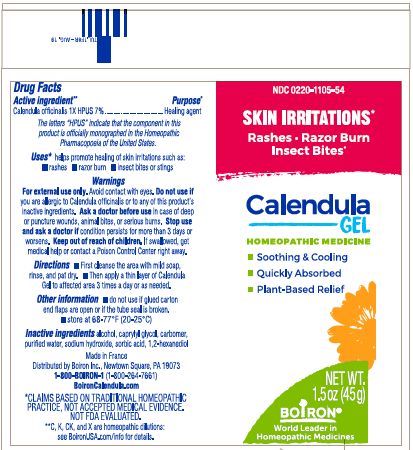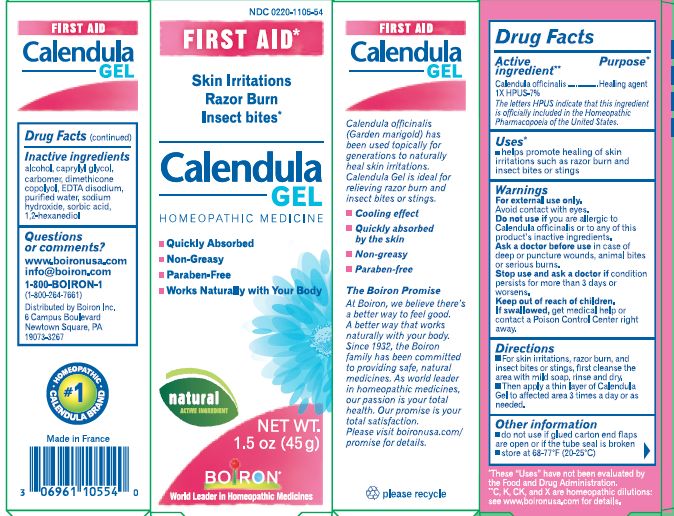 DRUG LABEL: Calendula
NDC: 0220-1105 | Form: GEL
Manufacturer: Laboratoires Boiron
Category: homeopathic | Type: HUMAN OTC DRUG LABEL
Date: 20240222

ACTIVE INGREDIENTS: CALENDULA OFFICINALIS FLOWERING TOP 1 [hp_X]/1 g
INACTIVE INGREDIENTS: ALCOHOL; CAPRYLYL GLYCOL; CARBOMER HOMOPOLYMER TYPE C; WATER; SODIUM HYDROXIDE; SORBIC ACID; 1,2-HEXANEDIOL

Calendula Gel 1.5oz

Active ingredients**

Calendula officinalis 1X HPUS 7%

The letters "HPUS" indicate that the components in this product are officially monographed in the Homeopathic Pharmacopoeia of the United States.

Purpose*

Calendula officinalis 1X HPUS 7% ... Healing agent

Uses*

helps promote healing of skin irritations such as:

- rashes
- razor burns
- insect bites or stings

WARNINGS

For external use only. Avoid contact with eyes.

Do not use if you are allergic to Calendula officinalis or to any of this product's inactive ingredients.

Ask a doctor before use in case of deep or puncture wounds, animal bites, or serious burns.

Stop use and ask doctor if condition persists for more than 3 days or worsens.

Keep out of reach of children. If swallowed, get medical help or contact a Poison Control Center right away.

DOSAGE AND ADMINISTRATION

- First cleanse the area with mild soap, rinse and dry.
- Then apply a thin layer of Calendula Gel to affected area 3 times a day or as needed.

INACTIVE INGREDIENT

alcohol, caprylyl glycol, carbomer, purified water, sodium hydroxide, sorbic acid, 1,2-hexanediol

QUESTIONS

BoironCalendula.com

BoironUSA.com

info@boironusa.com

1-800-BOIRON-1

1-800-264-7661)
Distributed by Boiron, Inc.

Newtown Square, PA 19073

Made in France

do not use if glued carton end flaps are open or if the tube seal is broken

store at 68-77o F (20-25o C)

Skin Irritations*

Rashes Razor Burn Insect Bites*

For all ages

1.5 oz (45 g)

*CLAIMS BASED ON TRADITIONAL HOMEOPATHIC PRACTICE, NOT ACCEPTED MEDICAL EVIDENCE. NOT FDA EVALUATED.

**C, K, CK, and X are homeopathic dilutions: see BoironUSA.com/info for details.